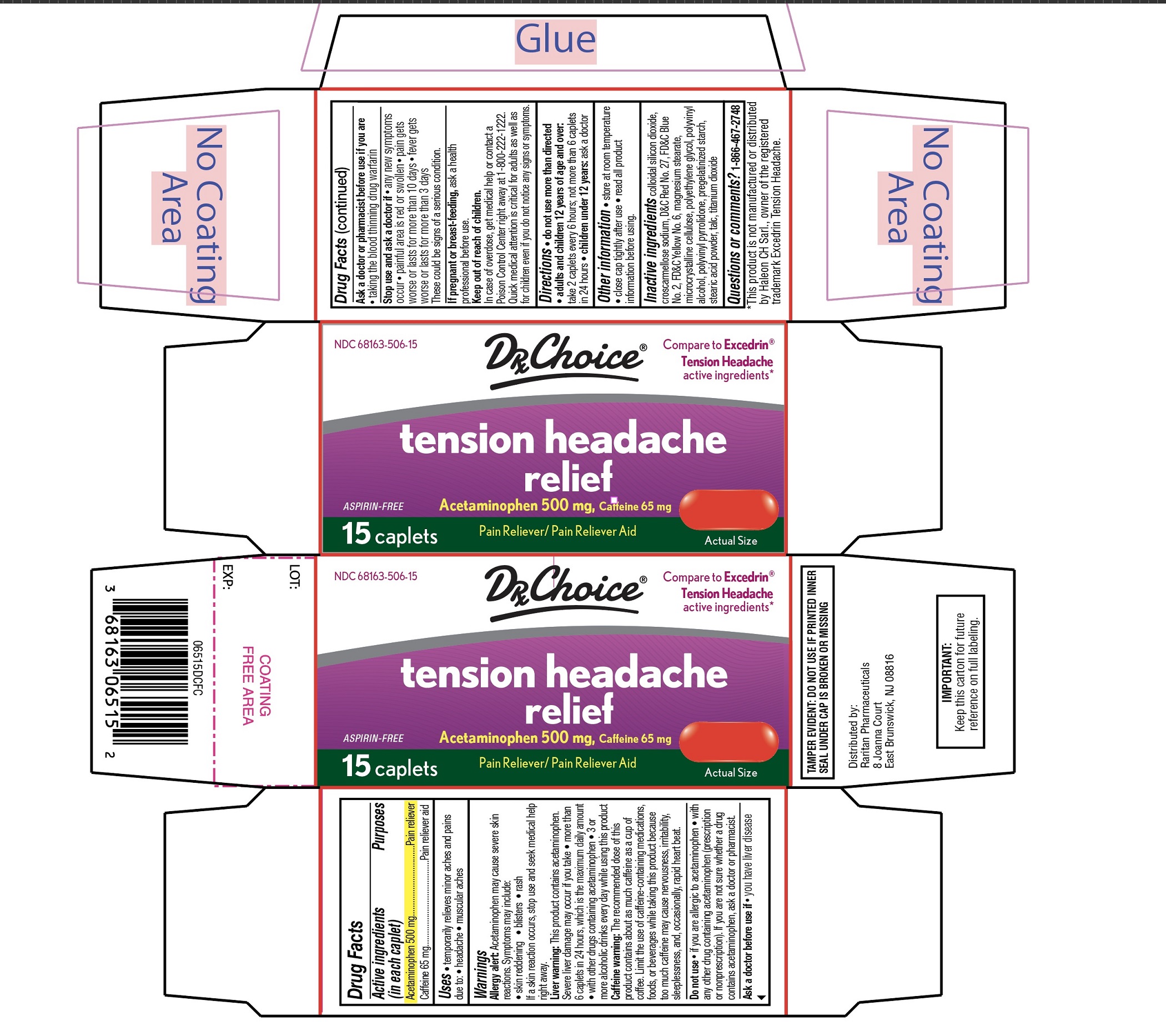 DRUG LABEL: DRX CHOICE

NDC: 68163-506 | Form: TABLET, FILM COATED
Manufacturer: Raritan Pharmaceuticals Inc.
Category: otc | Type: HUMAN OTC DRUG LABEL
Date: 20250613

ACTIVE INGREDIENTS: ACETAMINOPHEN 500 mg/1 1; CAFFEINE 65 mg/1 1
INACTIVE INGREDIENTS: SILICON DIOXIDE; CROSCARMELLOSE SODIUM; D&C RED NO. 27 ALUMINUM LAKE; FD&C BLUE NO. 2; FD&C YELLOW NO. 6; MAGNESIUM STEARATE; MICROCRYSTALLINE CELLULOSE; POLYETHYLENE GLYCOL, UNSPECIFIED; POLYVINYL ALCOHOL, UNSPECIFIED; EICOSYL POVIDONE; STARCH, CORN; STEARIC ACID; TALC; TITANIUM DIOXIDE

DRx Choice Tension Headache relief Drug Facts

Active ingredients (in each caplet)

Acetaminophen 500 mg

Caffeine 65 mg

Purposes

Pain reliever

Pain reliever aid

Uses

- temporarily relieves minor aches and pain due to:
- headache
- muscular aches

Warnings

Allergy alert: Acetaminophen may cause severe skin reactions. Symptoms may include:

- skin reddening
- blisters
- rash

If a skin reaction occurs, stop use and seek medical help right away.

Liver warning:

- This product contains acetaminophen. Severe liver damage may occur if you take

- more than 6 caplets in 24 hours, which is the maximum daily amount
- with other drugs containing acetaminophen
- 3 or more alcoholic drinks every day while using this product

Caffeine warning:

The recommended dose of this product contains about as much caffeine as a cup of coffee. Limit the use of caffeine-containing medications, foods, or beverages while taking this product because too much caffeine may cause nervousness, irritability, sleeplessness, and occasionally, rapid heartbeat.

Do not use

- if you are allergic to acetaminophen
- with any other drug containing acetaminophen (prescription or nonprescription). If you are not sure whether a drug contains acetaminophen, ask a doctor or pharmacist.

Ask a doctor before use if

- you have liver disease

Ask a doctor or pharmacist before use if you are

- taking the blood thinning drug warfarin

Stop use and ask a doctor if

- any new symptoms occur
- painful area is red or swollen
- pain gets worse or lasts for more than 10 days
- fever gets worse or lasts for more than 3 days

These could be signs of a serious condition.

If pregnant or breast-feeding,

ask a health professional before use.

Keep out of reach of children.

In case of overdose, get medical help or contact a Poison Control Center right away at 1-800-222-1222. Quick medical attention is critical for adults as well as for children even if you do not notice any signs or symptoms.

Directions

- do not use more than directed
- adults and children 12 years and over: take 2 caplets every 6 hours; not more than 6 caplets in 24 hours
- children under 12 years: ask a doctor

Other information

- store at room temperature
- close cap tightly after use
- read all product information before using.

Inactive ingredients

Colloidal silicon dioxide, croscarmellose sodium, D&C red no. 27, FD&C blue no. 2, FD&C yellow no. 6, magnesium stearate, microcrystalline cellulose, polyethylene glycol, polyvinyl alcohol, polyvinyl pyrrolidone, pregelatinized starch, stearic acid, talc, titanium dioxide

Questions or comments?

1-866-467-2748

Principal Display Panel

Compare to Excedrin® Tension Headacheactive ingredients *

NDC 68163-506-15

DRx Choice

tension headache

relief

ASPIRIN-FREE

Acetaminophen 500 mg,Caffeine 65 mg

Pain Reliever / Pain Reliever Aid

ACTUAL SIZE

15 CAPLETS

TAMPER-EVIDENT: DO NOT USE IF PRINTED INNER SEAL UNDER CAP IS BROKEN OR MISSING.

IMPORTANT:Keep this carton for future reference on full labeling.

Distributed by: Raritan Pharmaceuticals

8 Joanna Court

East Brunswick, NJ 08816

*This product is not manufactured or distributed by Haleon CH Sarl., owner of the registered trademark Excedrin Tension Headache.